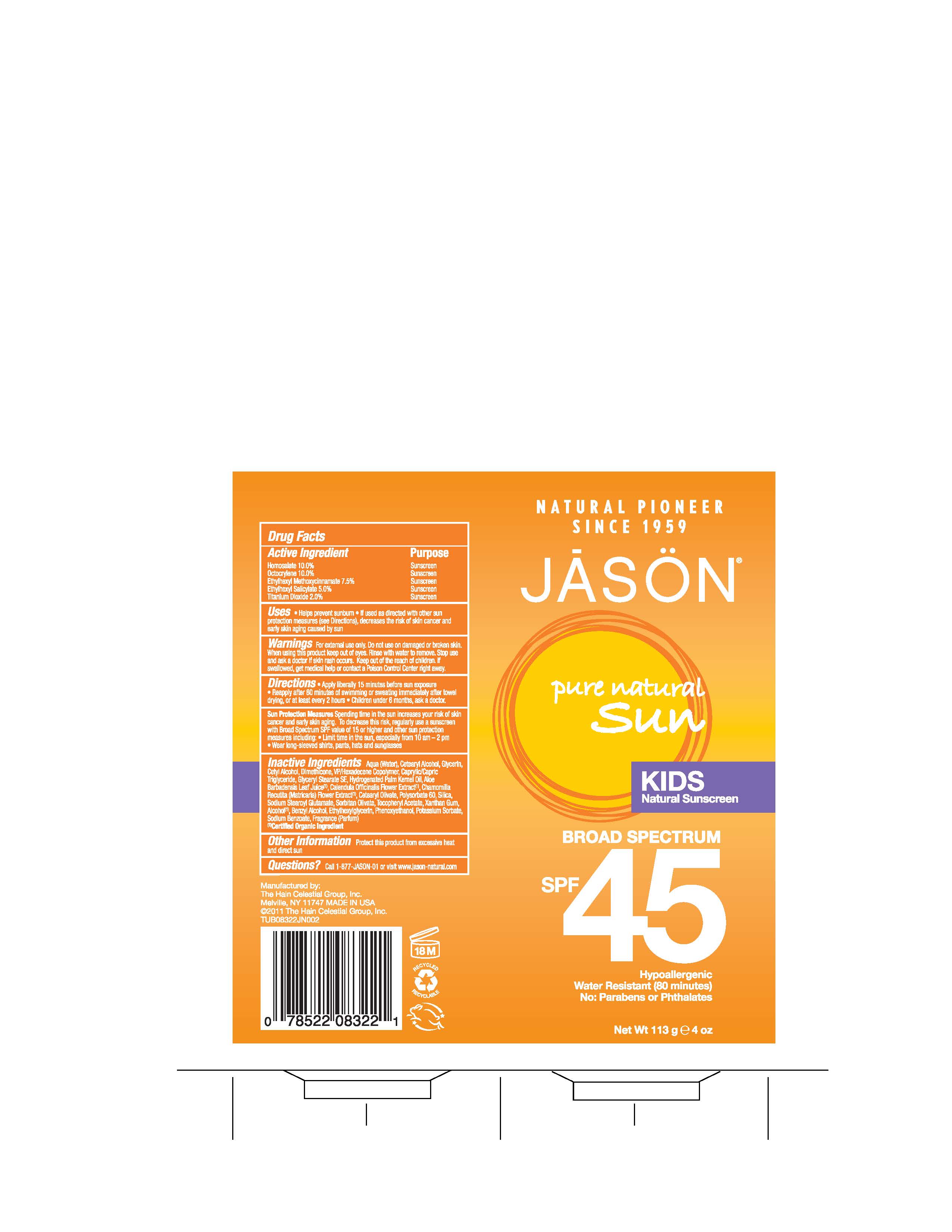 DRUG LABEL: Jason Pure Natural Sun Kids Natural Sunscren Broad Spectrum SPF45
                
NDC: 61995-0322 | Form: LOTION
Manufacturer: The Hain Celestial Group, Inc.
Category: otc | Type: HUMAN OTC DRUG LABEL
Date: 20120731

ACTIVE INGREDIENTS: HOMOSALATE 10 g/100 g; OCTOCRYLENE 10 g/100 g; OCTINOXATE 7.5 g/100 g; OCTISALATE  5.0 g/100 g; TITANIUM DIOXIDE  2.0 g/100 g
INACTIVE INGREDIENTS: WATER; CETOSTEARYL ALCOHOL; GLYCERIN ; CETYL ALCOHOL; DIMETHICONE; MEDIUM-CHAIN TRIGLYCERIDES; GLYCERYL STEARATE SE ; HYDROGENATED PALM KERNEL OIL ; ALOE VERA LEAF ; CALENDULA OFFICINALIS FLOWER  ; CHAMOMILE ; CETEARYL OLIVATE; POLYSORBATE 60; SILICON DIOXIDE; SODIUM STEAROYL GLUTAMATE; SORBITAN OLIVATE; .ALPHA.-TOCOPHEROL ACETATE ; XANTHAN GUM; ALCOHOL; BENZYL ALCOHOL ; ETHYLHEXYLGLYCERIN; PHENOXYETHANOL; POTASSIUM SORBATE; SODIUM BENZOATE

Drug Facts

ACTIVE INGREDIENT

Homosalate 10.0%

Octocrylene 10.0%

Ethylhexyl Methoxycinnamate 7.5%

Ethylhexyl Salicylate 5.0%

Titanium Dioxide 2.0%

PURPOSE

Sunscreens

INDICATIONS AND USAGE

- Helps prevent sunburns
- If used as directed with other sun protection measures, decreases the risk of skin cancer and early skin aging, caused by the sun.

WARNINGS

For external use only. Do not use on damaged or broken skin. When using this product keep out of eyes. Rinse with water to remove. Stop use and ask doctor if skin rash occurs.

Keep out of reach of children. If swallowed, get medical help or contact a Poison Control Center right away.

DOSAGE AND ADMINISTRATION

- Apply liberally 15 minutes before sun exposure. Reapply after 80 minutes of swimming or sweating after towel drying, or at least every 2 hours. Children under 6 months, ask a doctor. Skin Protection Measures: Spending time in the sun increases your risk of skin cancer and early skin aging. To decrease the risk, regularly use a sunscreen with Broad Spectrum SPF15 or higher and other protective measures including:
- Limit time in the sun, especially from 10am to 2pm
- Wear long-sleeved shirts, pants, hats and sunglasses.

INACTIVE INGREDIENT

Aqua (Water), Cetearyl Alcohol, Glycerin, Cetyl Alcohol, Dimethicone, VP/Hexadecene Copolymer, Caprylic/Capric Triglyceride, Glyceryl Stearate SE, Hydrogenated Palm Kernel Oil, Aloe Barbadensis Leaf Juice (1), Calendula Officinalis Flower Extract (1), Chamomilla Recutita (Matricaria) Flower Extract (1), Cetearyl Olivate, Polysorbate 60, Silica, Sodium Stearoyl Glutamate, Sorbitan Olivate, Tocopheryl Acetate, Xanthan Gum, Alcohol (1), Benzyl Alcohol, Ethylhexylglycerin, Phenoxyethanol, Potassium Sorbate, Sodium Benzoate, Fragrance (Parfum).

QUESTIONS

Questions? Call 1-877-JASON-01 or visit www.jason-natural.com